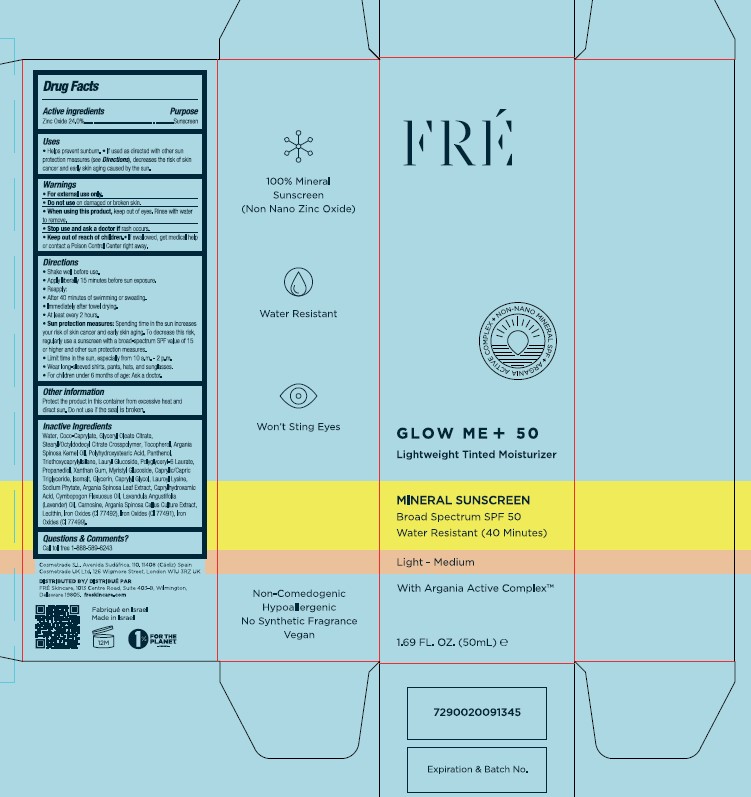 DRUG LABEL: FRE Glow ME Lightweight Tinted Moisturizer
NDC: 69435-1407 | Form: CREAM
Manufacturer: Peer Pharm Ltd
Category: otc | Type: HUMAN OTC DRUG LABEL
Date: 20260112

ACTIVE INGREDIENTS: ZINC OXIDE 24 g/100 mL
INACTIVE INGREDIENTS: COCO-CAPRYLATE; POLYGLYCERYL-6 LAURATE; LAUROYL LYSINE; CAPRYLHYDROXAMIC ACID; WATER; PANTHENOL; MYRISTYL GLUCOSIDE; LECITHIN, SOYBEAN; LAURYL GLUCOSIDE; PROPANEDIOL; TOCOPHEROL; ARGAN OIL; TRIETHOXYCAPRYLYLSILANE; ISOMALT; GLYCERIN; ARGANIA SPINOSA LEAF; EAST INDIAN LEMONGRASS OIL; GLYCERYL MONOOLEATE CITRATE; STEARYL/OCTYLDODECYL CITRATE CROSSPOLYMER; LAVENDER OIL; ARGANIA SPINOSA WHOLE; FERRIC OXIDE YELLOW; XANTHAN GUM; MEDIUM-CHAIN TRIGLYCERIDES; CAPRYLYL GLYCOL; CARNOSINE; PHYTATE SODIUM; FERRIC OXIDE RED; FERROSOFERRIC OXIDE; POLYHYDROXYSTEARIC ACID (2300 MW)

FRE GLOW ME + 50 MINERAL SUNSCREEN SPF 50

Drug Facts

Active Ingredient:

Zinc Oxide 24.0%

Purpose

SUNSCREEN

Uses

•Helps prevent sunburn.

• If used as directed with other sun
protection measures (see Directions), decreases the risk of skin
cancer and early skin aging caused by the sun

Warnings

• For external use only.
• Do not use on damaged or broken skin.
• When using this product, keep out of eyes. Rinse with water
to remove.
• Stop use and ask a doctor if rash occurs.
• If swallowed, get medical help
or contact a Poison Control Center right away.

Directions

• Shake well before use.
• Apply liberally 15 minutes before sun exposure.
• Reapply:
• After 40 minutes of swimming or sweating.
• Immediately after towel drying.
• At least every 2 hours.
• Sun protection measures: Spending time in the sun increases
your risk of skin cancer and early skin aging. To decrease this risk,
regularly use a sunscreen with a broad-spectrum SPF value of 15
or higher and other sun protection measures.
• Limit time in the sun, especially from 10 a.m. - 2 p.m.
• Wear long-sleeved shirts, pants, hats, and sunglasses.
• For children under 6 months of age: Ask a doctor.

Other information

Protect the product in this container from excessive heat and
direct sun. Do not use if the seal is broken.

Inactive Ingredients

Water, Coco-Caprylate, Glyceryl Oleate Citrate,
Stearyl/Octyldodecyl Citrate Crosspolymer, Tocopherol, Argania
Spinosa Kernel Oil, Polyhydroxystearic Acid, Panthenol,
Triethoxycaprylylsilane, Lauryl Glucoside, Polyglyceryl-6 Laurate,
Propanediol, Xanthan Gum, Myristyl Glucoside, Caprylic/Capric
Triglyceride, Isomalt, Glycerin, Caprylyl Glycol, Lauroyl Lysine,
Sodium Phytate, Argania Spinosa Leaf Extract, Caprylhydroxamic
Acid, Cymbopogon Flexuosus Oil, Lavandula Angustifolia
(Lavender) Oil, Carnosine, Argania Spinosa Callus Culture Extract,
Lecithin, Iron Oxides (CI 77492), Iron Oxides (CI 77491), Iron
Oxides (CI 77499).

Questions or Comments

Call toll free 1-888-589-6243